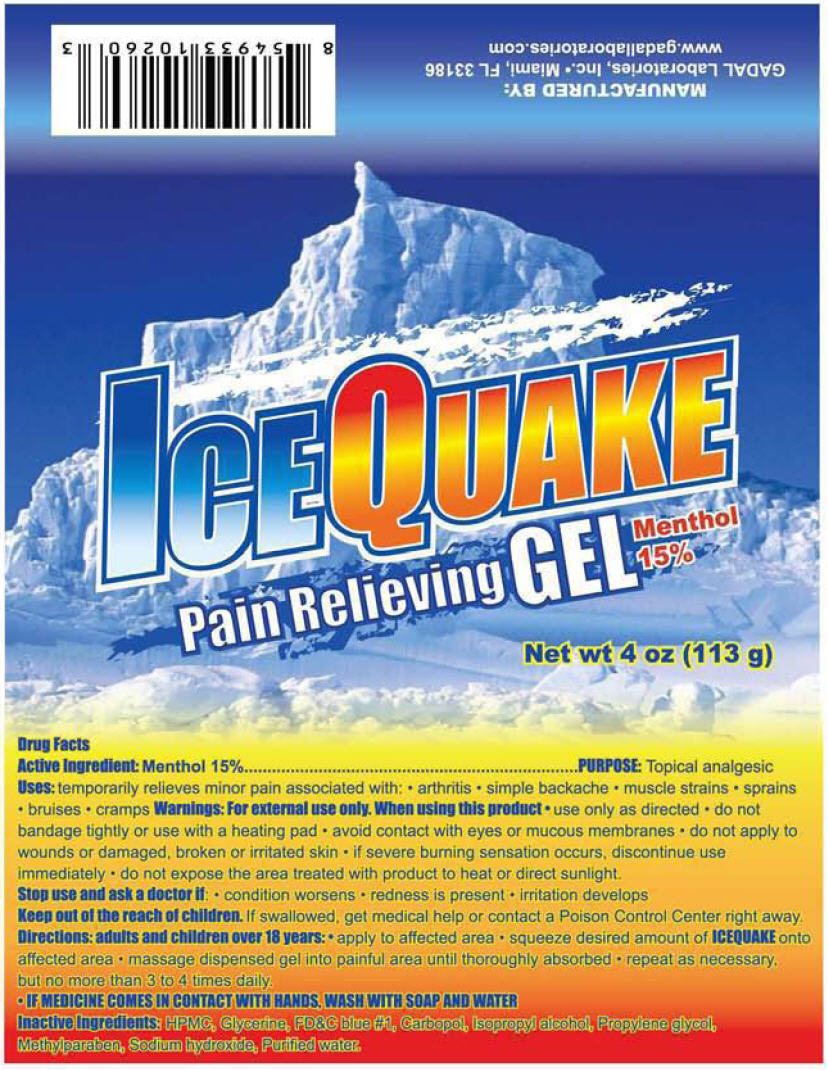 DRUG LABEL: Ice Quake
NDC: 53113-100 | Form: GEL
Manufacturer: Gadal Laboratories, Inc.
Category: otc | Type: HUMAN OTC DRUG LABEL
Date: 20120904

ACTIVE INGREDIENTS: Menthol 16.95 g/113 g
INACTIVE INGREDIENTS: HYPROMELLOSES; Glycerin; FD&C Blue NO. 1; Carbomer Homopolymer Type C (Allyl Pentaerythritol Crosslinked); Sodium Hydroxide; Water; Propylene Glycol; Methylparaben; Isopropyl Alcohol

Ice Quake

Drug Facts

Active Ingredient

Menthol 15%

PURPOSE

Topical analgesic

Uses

temporarily relieves minor pain associated with:

- arthritis
- simple backache
- muscle strains
- sprains
- bruises
- cramps

Warnings

For external use only.

When using this product

- use only as directed
- do not bandage tightly or use with a heating pad
- avoid contact with eyes or mucous membranes
- do not apply to wounds or damaged, broken or irritated skin
- if severe burning sensation occurs, discontinue use immediately
- do not expose the area treated with product to heat or direct sunlight.

Stop use and ask a doctor if:

- condition worsens
- redness is present
- irritation develops

KEEP OUT OF REACH OF CHILDREN

Keep out of the reach of children. If swallowed, get medical help or contact a Poison Control Center right away.

Directions

adults and children over 18 years:

- apply to affected area
- squeeze desired amount of ICEQUAKE onto affected area
- massage dispensed gel into painful area until thoroughly absorbed
- repeat as necessary, but no more than 3 to 4 times daily.

- IF MEDICINE COMES IN CONTACT WITH HANDS, WASH WITH SOAP AND WATER

Inactive Ingredients

HPMC, Glycerine, FD&C blue #1, Carbopol, Isopropyl alcohol, Propylene glycol, Methylparaben, Sodium hydroxide, Purified water.

MANUFACTURED BY:
GADAL Laboratories, Inc.• Miami, FL 33186

PRINCIPAL DISPLAY PANEL - 113 g Tube Label

ICEQUAKE
Pain Relieving GEL
Menthol
15%

Net wt 4 oz (113 g)